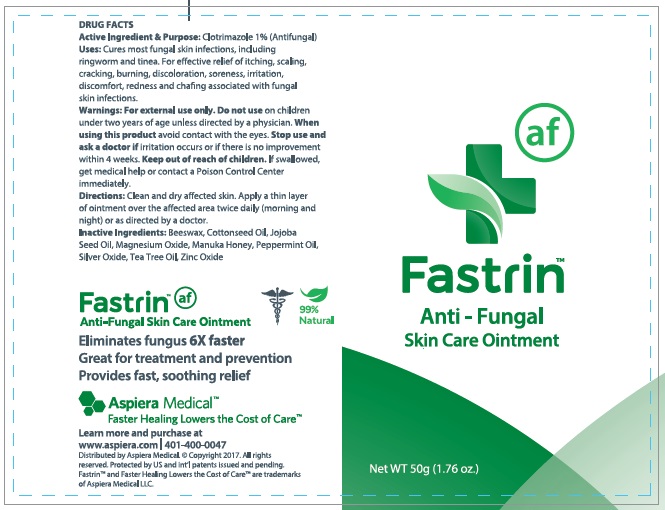 DRUG LABEL: Fastrin Anti - Fungal Skin Care
NDC: 24909-601 | Form: OINTMENT
Manufacturer: Aidance Skincare & Topical Solutions, LLC
Category: otc | Type: HUMAN OTC DRUG LABEL
Date: 20170601

ACTIVE INGREDIENTS: CLOTRIMAZOLE 1.0 g/100 g
INACTIVE INGREDIENTS: COTTONSEED OIL; HONEY; JOJOBA OIL; MAGNESIUM OXIDE; PEPPERMINT OIL; SILVER OXIDE; TEA TREE OIL; WHITE WAX; ZINC OXIDE

Drug Facts

Active Ingredient

Clotrimazole 1%

Purpose

Antifungal

Uses

Cures most fungal skin infections, including ringworm and tinea. For effective relief of itching, scaling, cracking, burning, discoloration, soreness, irritation, discomfort, redness and chafing associated with fungal skin infections.

Warnings

For external use only. Do not use on children under two years of age unless directed by a physician. When using this product avoid contact with the eyes. Stop use and ask a doctor if irritation occurs or if there is no improvement within 4 weeks.

Keep out of reach of children.

If swallowed, get medical help or contact a Poison Control Center immediately.

Directions

Clean and dry affected skin. Apply a thin layer of ointment over the affected area twice daily (morning and night) or as directed by a doctor.

Inactive Ingredients

Beeswax, Cottonseed Oil, Jojoba Seed Oil, Magnesium Oxide, Manuka Honey, Peppermint Oil, Silver Oxide, Tea Tree Oil, Zinc Oxide

PRINCIPAL DISPLAY PANEL - 50g Tube

Fastrin

Anti - Fungal

Skin Care Ointment

Net WT 50g (1.76 oz.)